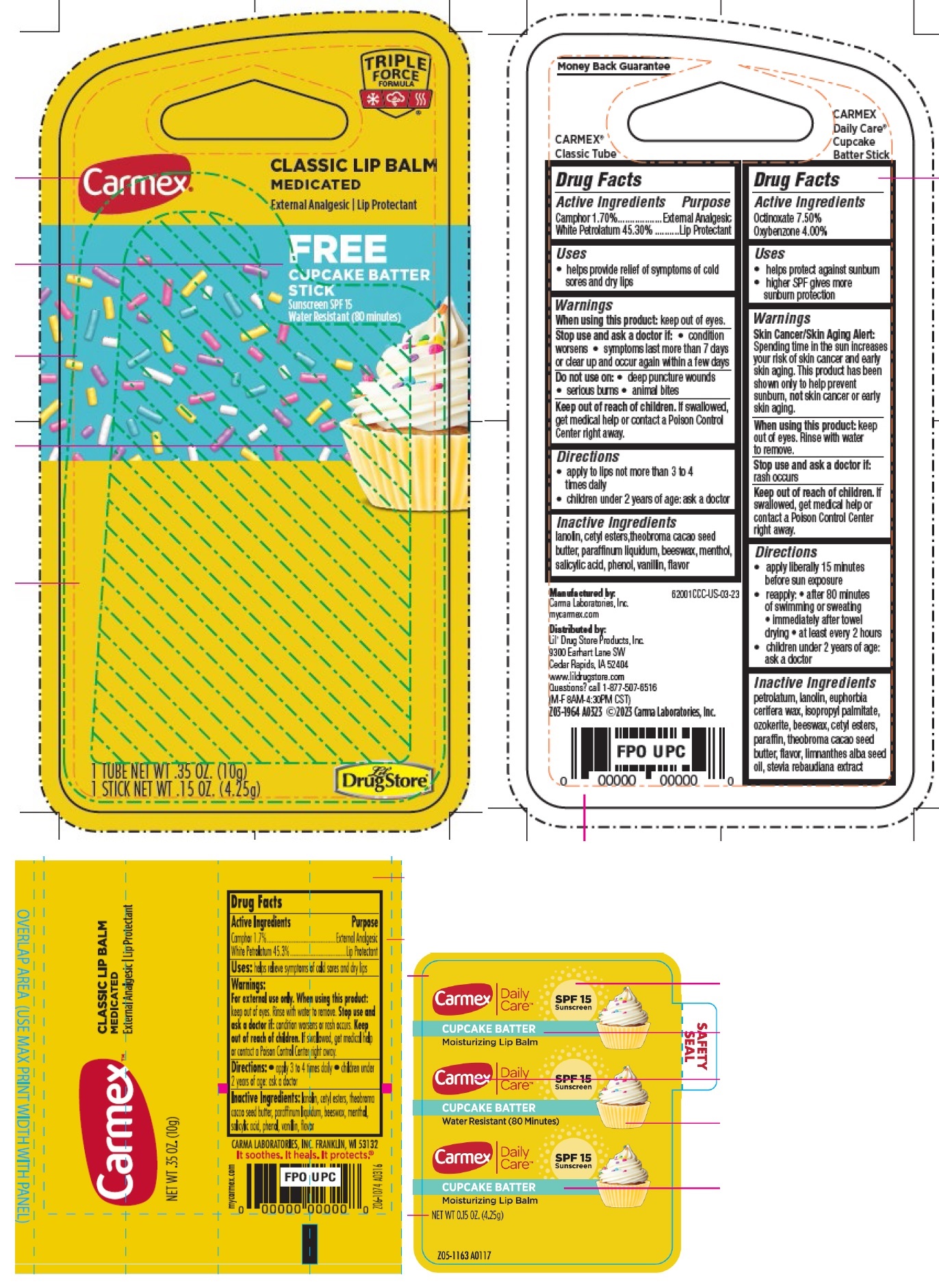 DRUG LABEL: Carmex Classic Lip Balm Medicated Free Cupcake Batter Stick Sunscreen SPF 15
NDC: 10210-0060 | Form: KIT | Route: TOPICAL
Manufacturer: Carma Laboratories, Inc.
Category: otc | Type: HUMAN OTC DRUG LABEL
Date: 20231205

ACTIVE INGREDIENTS: CAMPHOR (SYNTHETIC) 1.7 g/100 g; WHITE PETROLATUM 45.3 g/100 g; OCTINOXATE 75 mg/1 g; OXYBENZONE 40 mg/1 g
INACTIVE INGREDIENTS: LANOLIN; YELLOW WAX; CETYL ESTERS WAX; MINERAL OIL; MENTHOL; SALICYLIC ACID; PHENOL; VANILLIN; PETROLATUM; LANOLIN; ISOPROPYL PALMITATE; YELLOW WAX; CETYL ESTERS WAX; PARAFFIN; MEADOWFOAM SEED OIL

Carmex Classic Lip Balm Medicated Free Cupcake Batter Stick Sunscreen SPF 15

Active Ingredients

Camphor 1.70%

White Petrolatum 45.30%

Purpose

External Analgesic

Lip Protectant

Uses

- helps provide relief of symptoms of cold sores and dry lips

Warnings

For external use only

When using this product:

keep out of eyes. Rinse with water to remove.

Stop use and ask a doctor if:

- condition worsens
- symptoms last more than 7 days or clear up and occur again within a few days

Do not use on:

- deep puncture wounds
- serious burns
- animal bites

Keep out of reach of children.

If swallowed, get medical help or contact a Poison Control Center right away.

Directions

- apply to lips not more than 3 to 4 times daily
- children under 2 years of age: ask a doctor

Other Information

- this is a personal care item, and should be used by one individual only

Inactive Ingredients

lanolin, beeswax, cetyl esters, paraffinum liquidum, theobroma cacao seed butter, menthol, salicylic acid, phenol, vanillin, flavor

Active Ingredients

Octinoxate 7.50%

Oxybenzone 4.00%

Purpose

Sunscreen

Uses

- helps protect against sunburn
- higher SPF gives more sunburn protection

Warnings

Skin Cancer/Skin Aging Alert:Spending time in the sun increases your risk of skin cancer and early skin aging. This product has been shown only to help prevent sunburn, notskin cancer or early skin aging.

For external use only

Do not use

on damaged or broken skin

When using this product:

keep out of eyes. Rinse with water to remove.

Stop use and ask a doctor if:

rash occurs

Keep out of reach of children.

If swallowed, get medical help or contact a Poison Control Center right away.

Directions

apply liberally 15 minutes before sun exposure

reapply: • after 80 minutes of swimming or sweating • immediately after towel drying • at least every 2 hours

• children under 2 years of age: ask a doctor

Other Information

• this is personal care item, and should be used by one individual only

• protect this product from excessive heat and direct sun

Inactive Ingredients

petrolatum, lanolin, euphorbia cerifera wax, isopropyl palmitate, ozokerite, beeswax, cetyl esters, paraffin, theobroma cacao seed butter, flavor, limnanthes alba seed oil, stevia rebaudiana extract